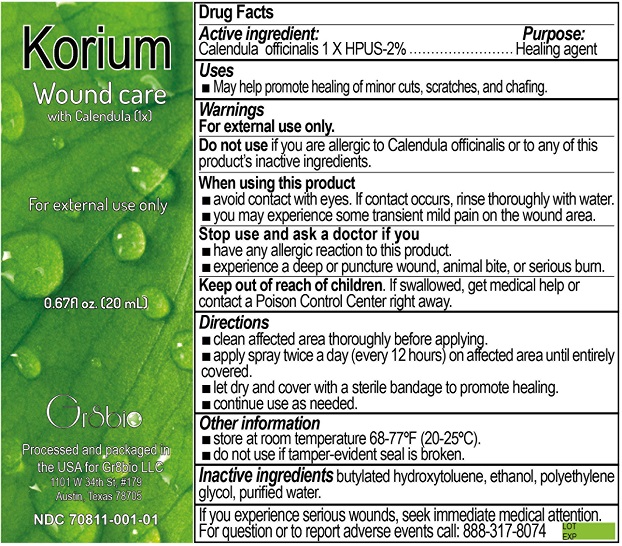 DRUG LABEL: Korium
NDC: 70811-001 | Form: SPRAY
Manufacturer: GR8BIO LLC
Category: homeopathic | Type: HUMAN OTC DRUG LABEL
Date: 20200124

ACTIVE INGREDIENTS: CALENDULA OFFICINALIS WHOLE 1 [hp_X]/20 mL
INACTIVE INGREDIENTS: WATER; BUTYLATED HYDROXYTOLUENE; ALCOHOL; POLYETHYLENE GLYCOL, UNSPECIFIED

Korium

ACTIVE INGREDIENT

Calendula Officinalis 1X HPUS -2%

PURPOSE

Healing Agent

INDICATIONS AND USAGE

May help promote healing of minor cuts, scratches and chafing.

WARNINGS

FOR EXTERNAL USE ONLY

DO NOT USE if you are allergic to Calendula officinalis or to any of this product's inactive ingredients.

WHEN USING THIS PRODUCT:

Avoid contact with eyes. If contact occurs, rinse thoroughly with water.

You may experience some transient mild pain on the wound area.

STOP USE AND ASK DOCTOR IF YOU:

Have any allergic reaction to this product.

Experience a deep or puncture wound, animal bite, or serious burn.

KEEP OUT OF REACH OF CHILDREN

KWEEP OUT OF REACH OF CHILDREN. If swallowed get medical help or contact a poison control center right away.

DIRECTIONS

- clean affected area thoroughly before applying
- apply spray twice a day (every 12 hours) on affected area until entirely covered.
- let dry and cover with a sterile bandage to promote healing.
- continue use as needed

OTHER INFORMATION

Store at room temperature 68-77°F (20-25°C).

Do not use if tamper evident seal is broken.

INACTIVE INGREDIENT

Butylated Hydroxytoluene

Ethanol

Polyethylene Glycol

Purified Water